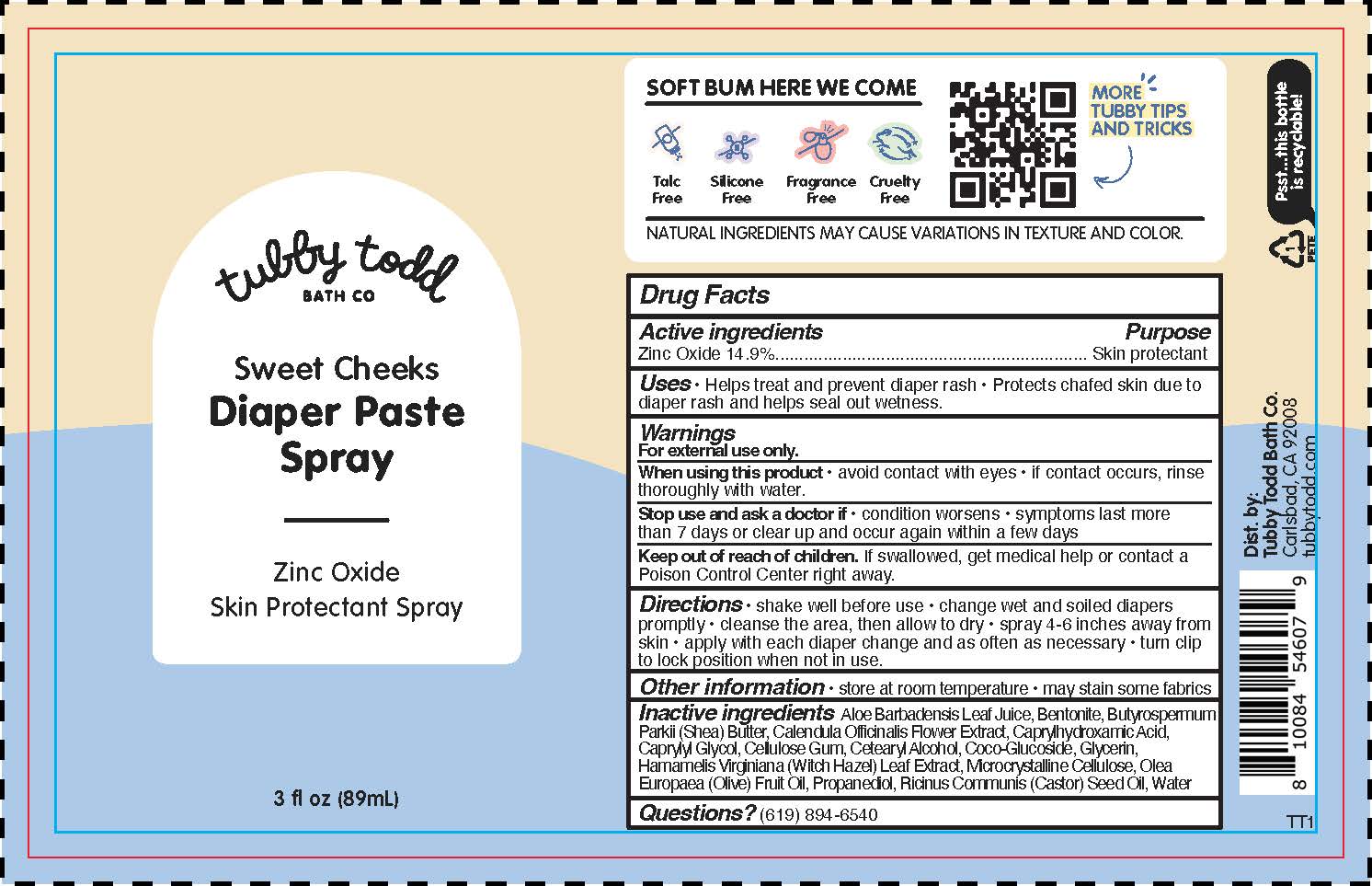 DRUG LABEL: Sweet Cheeks Diaper Sprayer
NDC: 73088-304 | Form: SPRAY
Manufacturer: Tubby Todd
Category: otc | Type: HUMAN OTC DRUG LABEL
Date: 20241223

ACTIVE INGREDIENTS: ZINC OXIDE 14.9 g/100 g
INACTIVE INGREDIENTS: BENTONITE; CELLULOSE GUM; GLYCERIN; OLEA EUROPAEA (OLIVE) FRUIT OIL; RICINUS COMMUNIS (CASTOR) SEED OIL; CAPRYLHYDROXAMIC ACID; CAPRYLYL GLYCOL; COCO-GLUCOSIDE; MICROCRYSTALLINE CELLULOSE; PROPANEDIOL; WATER; HAMAMELIS VIRGINIANA LEAF; ALOE BARBADENSIS LEAF JUICE; BUTYROSPERMUM PARKII (SHEA) BUTTER; CALENDULA OFFICINALIS FLOWER; CETEARYL ALCOHOL

Sweet Cheeks Diaper Paste Spray

Active ingredients

Zinc Oxide 14.9%

Purpose

Skin protectant

Uses

• helps treat and prevent diaper rash
• protects chafed skin due to diaper rash and helps seal out wetness

Warnings

For external use only.

When using this product

• do not use near eyes. In case of contact, rinse eyes thoroughly with water.

Stop use and ask a doctor if

• condition worsens • symptoms last more than 7 days or clear up and occur again within a few days

Keep out of reach of children.

If swallowed get medical help or contact a Poison Control Center immediately

Directions

• shake well before use
• change wet or soiled diapers promptly
• cleanse the diaper area and allow to dry
• spray 4-6 inches away from skin
• apply with each diaper change and as often as necessary
• turn clip to lock position when not in use.

Other information

• store at room temperature
• may stain some fabrics

Inactive ingredients

Aloe Barbadensis Leaf Juice, Bentonite, Butyrospermum Parkii (Shea) Butter, Calendula Officinalis Flower Extract, Caprylhydroxamic Acid, Caprylyl Glycol, Cellulose Gum, Cetearyl Alcohol, Coco-Glucoside, Glycerin, Hamamelis Virginiana (Witch Hazel) Leaf Extract, Microcrystalline Cellulose, Olea Europaea (Olive) Fruit Oil, Propanediol, Ricinus Communis (Castor) Seed Oil, Water